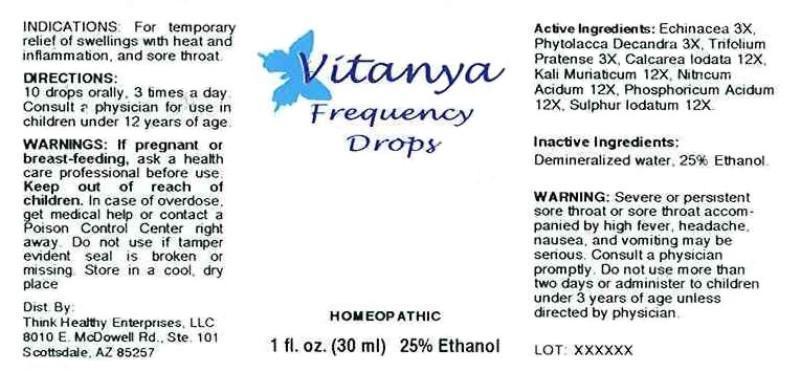 DRUG LABEL: VITANYA FREQUENCY
NDC: 58968-0001 | Form: LIQUID
Manufacturer: Think Healthy Enterprises, LLC.
Category: homeopathic | Type: HUMAN OTC DRUG LABEL
Date: 20141030

ACTIVE INGREDIENTS: ECHINACEA ANGUSTIFOLIA 3 [hp_X]/1 mL; PHYTOLACCA AMERICANA ROOT 3 [hp_X]/1 mL; TRIFOLIUM PRATENSE FLOWER 3 [hp_X]/1 mL; CALCIUM IODIDE 12 [hp_X]/1 mL; POTASSIUM CHLORIDE 12 [hp_X]/1 mL; NITRIC ACID 12 [hp_X]/1 mL; PHOSPHORIC ACID 12 [hp_X]/1 mL; SULFUR IODIDE 12 [hp_X]/1 mL
INACTIVE INGREDIENTS: WATER; ALCOHOL

DRUG FACTS:

ACTIVE INGREDIENTS:

ECHINACEA (ANGUSTIFOLIA) 3X, PHYTOLACCA DECANDRA 3X, TRIFOLIUM PRATENSE 3X, CALCAREA IODATA 12X, KALI MURIATICUM 12X, NITRICUM ACIDUM 12X, PHOSPHORICUM ACIDUM 12X, SULPHUR IODATUM 12X

INDICATIONS:

For temporary relief of swellings with heat and inflammation, and sore throat.

WARNINGS:

If pregnant or breast-feeding, ask a health care professional before use.

Keep out of reach of children. In case of overdose, get medical help or contact a Poison Control Center right away.

Do not use if tamper evident seal is broken or missing. Store in a cool, dry place.

WARNING: Severe or persistent sore throat accompanied by high fever, headache, nausea, and vomiting may be serious. Consult a physician promptly. Do not use more than two days or administer to children under 3 years of age unless directed by a physician.

Keep out of reach of children. In case of overdose, get medical help or contact a Poison Control Center right away.

DIRECTIONS:

10 drops orally, 3 times a day. Consult a physician for use in children under 12 years of age.

INDICATIONS:

For temporary relief of swellings with heat and inflammation, and sore throat.

INACTIVE INGREDIENTS:

Demineralized water, 25% Ethanol

QUESTIONS:

Dist. by:

Think Healthy Enterprises, LLC

8010 E. McDowell Rd., Ste. 101

Scottsdale, AZ 85257

PACKAGE LABEL DISPLAY:

Vitanya

Frequency

Drops

HOMEOPATHIC

1 fl. oz. (30 ml) 25% Ethanol